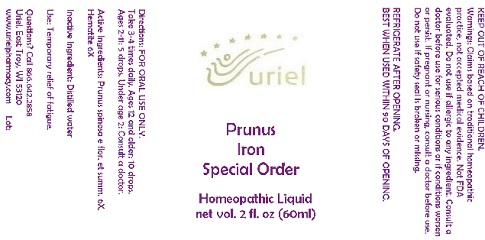 DRUG LABEL: Prunus Iron Special Order
NDC: 48951-8333 | Form: LIQUID
Manufacturer: Uriel Pharmacy Inc.
Category: homeopathic | Type: HUMAN OTC DRUG LABEL
Date: 20180509

ACTIVE INGREDIENTS: FERRIC OXIDE RED 6 [hp_X]/1 mL; PRUNUS SPINOSA FLOWER BUD 6 [hp_X]/1 mL
INACTIVE INGREDIENTS: WATER

Prunus Iron Special Order

INDICATIONS AND USAGE

Directions: FOR ORAL USE ONLY.

DOSAGE AND ADMINISTRATION

Take 3-4 times daily. Ages 12 and older: 10 drops.
Ages 2-11: 5 drops. Under age 2: Consult a doctor.

ACTIVE INGREDIENT

Active Ingredients: Prunus spinosa e flor. et summ. 6X, Hematite 6X

Inactive Ingredient: Distilled water

PURPOSE

Use: Temporary relief of fatigue.

KEEP OUT OF REACH OF CHILDREN.

WARNINGS

Warnings: Claims based on traditional homeopathic practice, not accepted medical evidence. Not FDA evaluated. Do not use if allergic to any ingredient. Consult a doctor before use for serious conditions or if conditions worsen or persist. If pregnant or nursing, consult a doctor before use. Do not use if safety seal is broken or missing.

REFRIGERATE AFTER OPENING.
BEST WHEN USED WITHIN 90 DAYS OF OPENING.

Questions? Call 866.642.2858
Uriel, East Troy, WI 53120
www.urielpharmacy.com